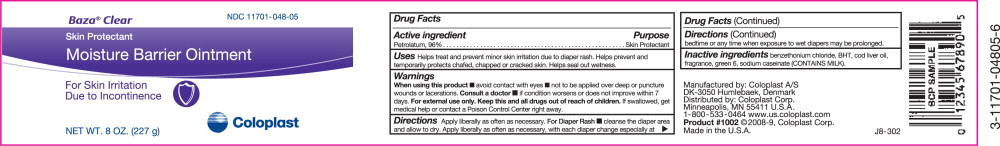 DRUG LABEL: Baza Clear
NDC: 11701-048 | Form: OINTMENT
Manufacturer: Coloplast Manufacturing US, LLC
Category: otc | Type: HUMAN OTC DRUG LABEL
Date: 20231220

ACTIVE INGREDIENTS: PETROLATUM 960 mg/1 g
INACTIVE INGREDIENTS: COD LIVER OIL; SODIUM CASEINATE; BENZETHONIUM CHLORIDE; BUTYLATED HYDROXYTOLUENE; D&C GREEN NO. 6

Baza® Clear
Skin Protectant
Moisture Barrier Ointment

For Skin Irritation Due to Incontinence

Drug Facts

Active ingredient

Petrolatum, 96%

Purpose

Skin Protectant

INDICATIONS AND USAGE

Uses Helps treat and prevent minor skin irritation due to diaper rash. Helps prevent and temporarily protects chafed, chapped or cracked skin. Helps seal out wetness.

Warnings

When using this product

- avoid contact with eyes
- not to be applied over deep or puncture wounds or lacerations.

Consult a doctor

- if condition worsens or does not improve within 7 days.

For external use only.

KEEP OUT OF REACH OF CHILDREN

Keep this and all drugs out of reach of children. If swallowed, get medical help or contact a Poison Control Center right away.

Directions

- apply liberally as often as necessary.

For Diaper Rash: cleanse the diaper area and allow to dry

- apply liberally as often as necessary, with each diaper change especially at bedtime or any time when exposure to wet diapers may be prolonged.

INACTIVE INGREDIENT

Inactive ingredients benzethonium chloride, BHT, cod liver oil, fragrance, green 6, sodium caseinate (CONTAINS MILK)

See crimp for lot no. and expiration date

Manufactured by: Coloplast A/S
DK-3050 Humlebaek, Denmark
Distributed by: Coloplast Corp.
Minneapolis, MN 55411 U.S.A.
1-800-533-0464 www.us.coloplast.com
Product #1006 ©2008-7, Coloplast Corp.
Made in the U.S.A.

G8-303

PACKAGE LABEL

PRINCIPAL DISPLAY PANEL - NET WT. 5 OZ. (142g)

NDC 11701-048-014

Baza® Clear

Skin Protectant

Moisture Barrier Ointment

For Skin Irritation Due to Incontinence

Coloplast

NET WT. 5 OZ. (142 g)